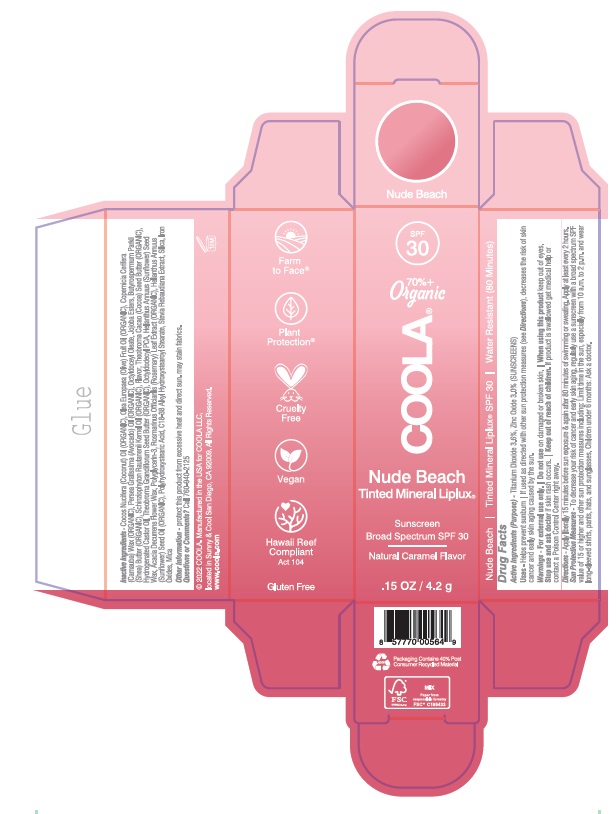 DRUG LABEL: COOLA Mineral Liplux Lip Balm SPF 30 Nude Beach
NDC: 79753-055 | Form: STICK
Manufacturer: COOLA, LLC
Category: otc | Type: HUMAN OTC DRUG LABEL
Date: 20240522

ACTIVE INGREDIENTS: TITANIUM DIOXIDE 3.6 g/100 g; ZINC OXIDE 3 g/100 g
INACTIVE INGREDIENTS: POLYHYDROXYSTEARIC ACID (2300 MW); SILICON DIOXIDE; MICA; ROSEMARY; SHEA BUTTER; JOJOBA OIL, RANDOMIZED; SUNFLOWER OIL; C18-38 ALKYL HYDROXYSTEAROYL STEARATE; STEVIA REBAUDIANA WHOLE; OCTYLDODECYL OLEATE; SCHINZIOPHYTON RAUTANENII SEED OIL; THEOBROMA GRANDIFLORUM SEED BUTTER; OLIVE OIL; HYDROGENATED CASTOR OIL; OCTYLDODECYL PCA; FERRIC OXIDE RED; COCONUT OIL; CARNAUBA WAX; AVOCADO OIL; COCOA BUTTER; HELIANTHUS ANNUUS SEED WAX; ACACIA DECURRENS FLOWER WAX; POLYGLYCERIN-3

COOLA Mineral Liplux Lip Balm SPF 30 - Nude Beach

ACTIVE INGREDIENT

Titanium Dioxide 3.6%

Zinc Oxide 3.0%

PURPOSE

Sunscreen

Uses

- Helps prevent sunburn
- If used as directed with other sun protection measures (see Directions), decreases the risk of skin cancer and early skin aging caused by the sun.

WARNINGS

- For external use only.
- Do not use on damaged or broken skin.
- When using this product keep out of eyes.
- Stop use and ask doctor if skin rash occurs

Keep out of reach of children. If product is swallowed get medical help or contact a Poison Control Center right away.

Directions

- Apply liberally 15 minutes before sun exposure & again after 80 minutes of swimming or sweating.
- Apply at least every 2 hours.
- Sun Protection Measures - To decrease your risk of cancer and early skin aging, regularly use a sunscreen with a broad spectrum SPF value of 15 or higher and other sun protection measures including: Limit time in the sun, especially from 10 a.m. to 2 p.m. and wear long-sleeved shirts, pants, hats, and sunglasses.

INACTIVE INGREDIENT

Cocos Nucifera (Coconut) Oil (ORGANIC), Olea Europaea (Olive) Fruit Oil (ORGANIC), Copernicia Cerifera (Carnauba) Wax (ORGANIC), Persea Gratissima (Avocado) Oil (ORGANIC), Octyldodecyl Oleate, Jojoba Esters, Butyrospermum Parkii (Shea) Butter (ORGANIC), Schinziophyton Rautanenii Kernel Oil (ORGANIC), Flavor, Theobroma Cacao (Cocoa) Seed Butter (ORGANIC), Hydrogenated Castor Oil, Theobroma Grandiflorum Seed Butter (ORGANIC), Octyldodecyl PCA, Helianthus Annuus (Sunflower) Seed Wax, Acacia Decurrens Flower Wax, Polyglycerin-3, Rosmarinus Officinalis (Rosemary) Leaf Extract (ORGANIC), Helianthus Annuus (Sunflower) Seed Oil (ORGANIC), Polyhydroxystearic Acid, C18-38 Alkyl Hydroxystearoyl Stearate, Stevia Rebaudiana Extract, Silica, Iron Oxides, Mica

OTHER SAFETY INFORMATION

Protect this product from excessive heat and direct sun.

QUESTIONS

Call 760-940-2125